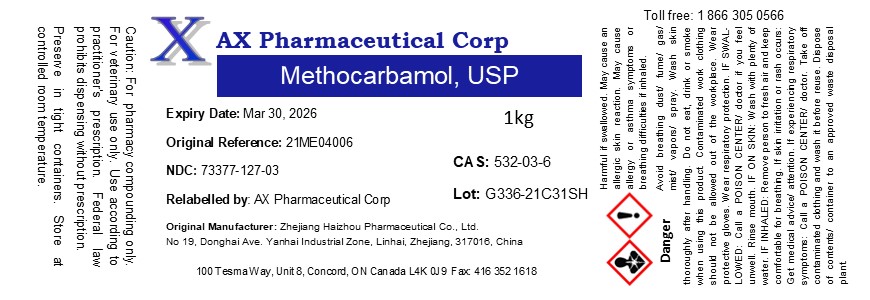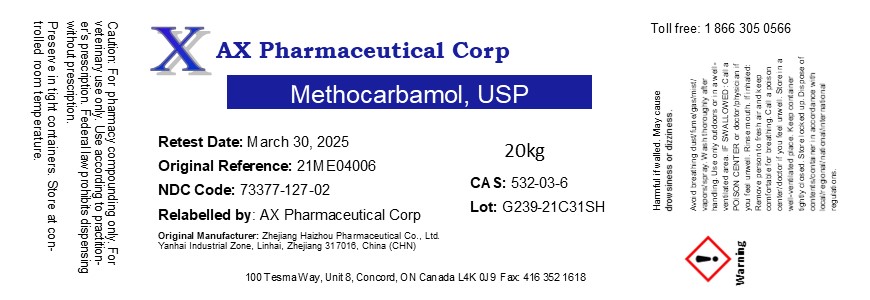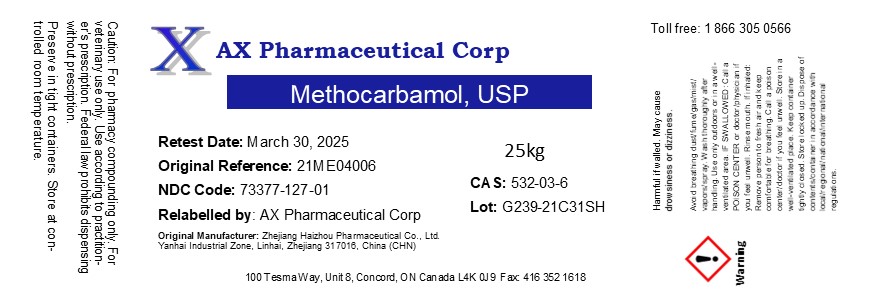 DRUG LABEL: Methocarbamol
NDC: 73377-127 | Form: POWDER
Manufacturer: AX Pharmaceutical Corp
Category: other | Type: BULK INGREDIENT - ANIMAL DRUG
Date: 20241209

ACTIVE INGREDIENTS: METHOCARBAMOL 1 kg/1 kg

Methocarbamol